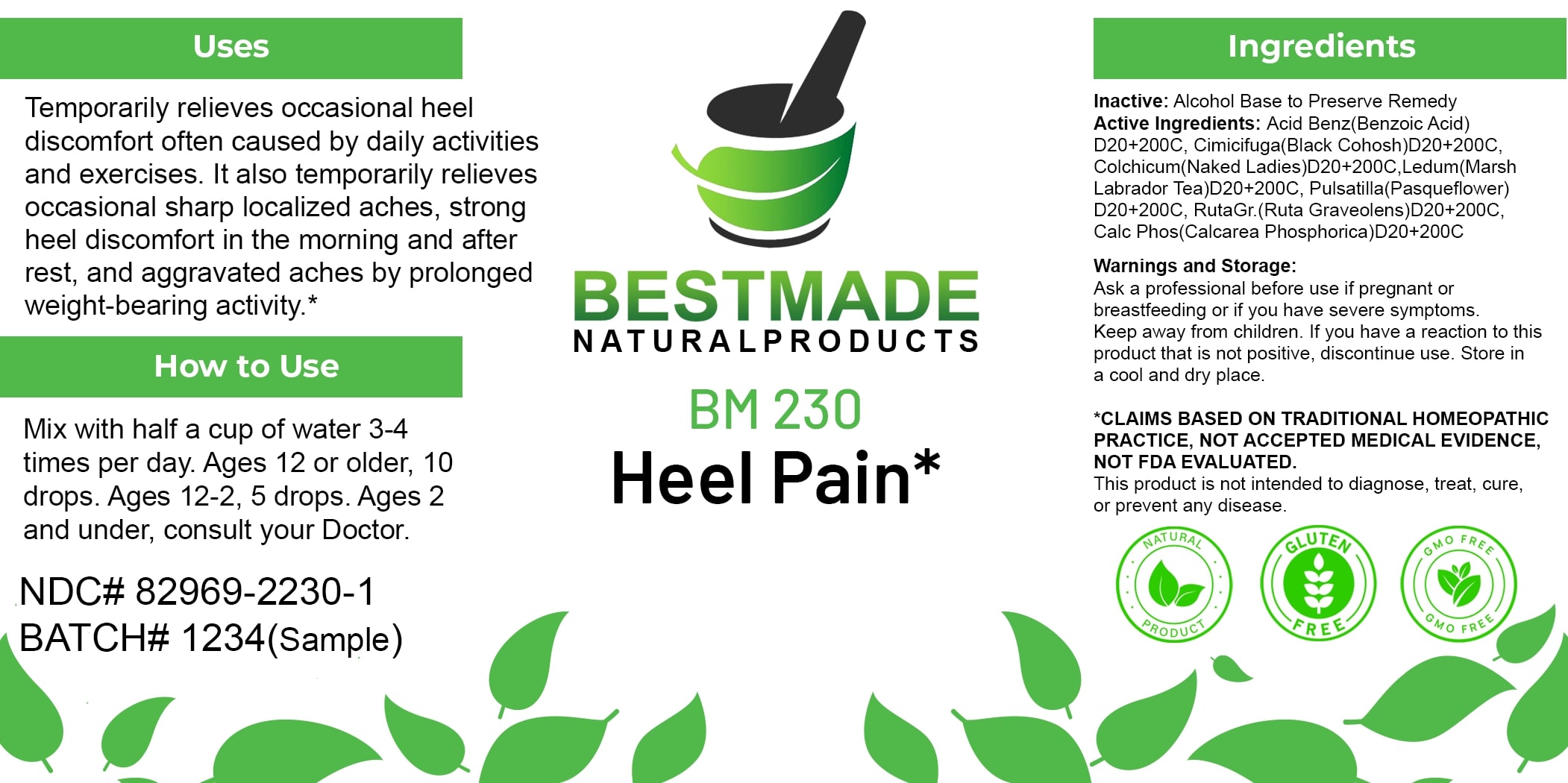 DRUG LABEL: Bestmade Natural Products BM230
NDC: 82969-2230 | Form: LIQUID
Manufacturer: Bestmade Natural Products
Category: homeopathic | Type: HUMAN OTC DRUG LABEL
Date: 20250304

ACTIVE INGREDIENTS: CIMICIFUGA RACEMOSA ROOT 200 [hp_C]/200 [hp_C]; RUTA GRAVEOLENS FLOWERING TOP 200 [hp_C]/200 [hp_C]; TRIBASIC CALCIUM PHOSPHATE 200 [hp_C]/200 [hp_C]; PULSATILLA VULGARIS 200 [hp_C]/200 [hp_C]; COLCHICUM AUTUMNALE BULB 200 [hp_C]/200 [hp_C]; BENZOIC ACID 200 [hp_C]/200 [hp_C]; LEDUM PALUSTRE TWIG 200 [hp_C]/200 [hp_C]
INACTIVE INGREDIENTS: ALCOHOL 200 [hp_C]/200 [hp_C]

BM230

DOSAGE AND ADMINISTRATION

How to Use

Mix with half a cup of water 3-4 times per day. Ages 12 or older, 10 drops. Ages 12-2, 5 drops. Ages 2 and under, consult your Doctor.

INACTIVE INGREDIENT

Ingredients

Inactive: Alcohol Base to Preserve Remedy

ACTIVE INGREDIENT

Active Ingredients: Acid Benz(Benzoic acid) D20+200C, Cimicifuga(Black Cohosh)D20+200C, Colchicum(Naked Ladies)D20+200C, Ledum(Marsh Labrador Tea)D20+200C, Pulsatilla(Pasqueflower) D20+200C, Ruta(Rue)D20+200C, Calc Phos(Calcarea Phosphorica)D20+200C

KEEP OUT OF REACH OF CHILDREN

Warnings and Storage:

Ask a professional before use if pregnant or breastfeeding or if you have severe symptoms. Keep away from children. If you have a reaction to this product that is not positive, discontinue use. Store in a cool and dry place.

Warnings and Storage:

Ask a professional before use if pregnant or breastfeeding or if you have severe symptoms. Keep away from children. If you have a reaction to this product that is not positive, discontinue use. Store in a cool and dry place.

*CLAIMS BASED ON TRADITIONAL HOMEOPATHIC PRACTICE, NOT ACCEPTED MEDICAL EVIDENCE. NOT FDA EVALUATED.

This product is not intended to diagnose, treat, cure, or prevent any disease.

Uses

Temporarily relieves occasional heel discomfort often caused by daily activities and exercises. It also temporarily relieves occasional sharp localized aches, strong heel discomfort in the morning and after rest, and aggravated aches by prolonged weight-bearing activity.*

*CLAIMS BASED ON TRADITIONAL HOMEOPATHIC PRACTICE, NOT ACCEPTED MEDICAL EVIDENCE. NOT FDA EVALUATED.

This product is not intended to diagnose, treat, cure, or prevent any disease.

Uses

Temporarily relieves occasional heel discomfort often caused by daily activities and exercises. It also temporarily relieves occasional sharp localized aches, strong heel discomfort in the morning and after rest, and aggravated aches by prolonged weight-bearing activity.*

*CLAIMS BASED ON TRADITIONAL HOMEOPATHIC PRACTICE, NOT ACCEPTED MEDICAL EVIDENCE. NOT FDA EVALUATED.

This product is not intended to diagnose, treat, cure, or prevent any disease.

Entire package label